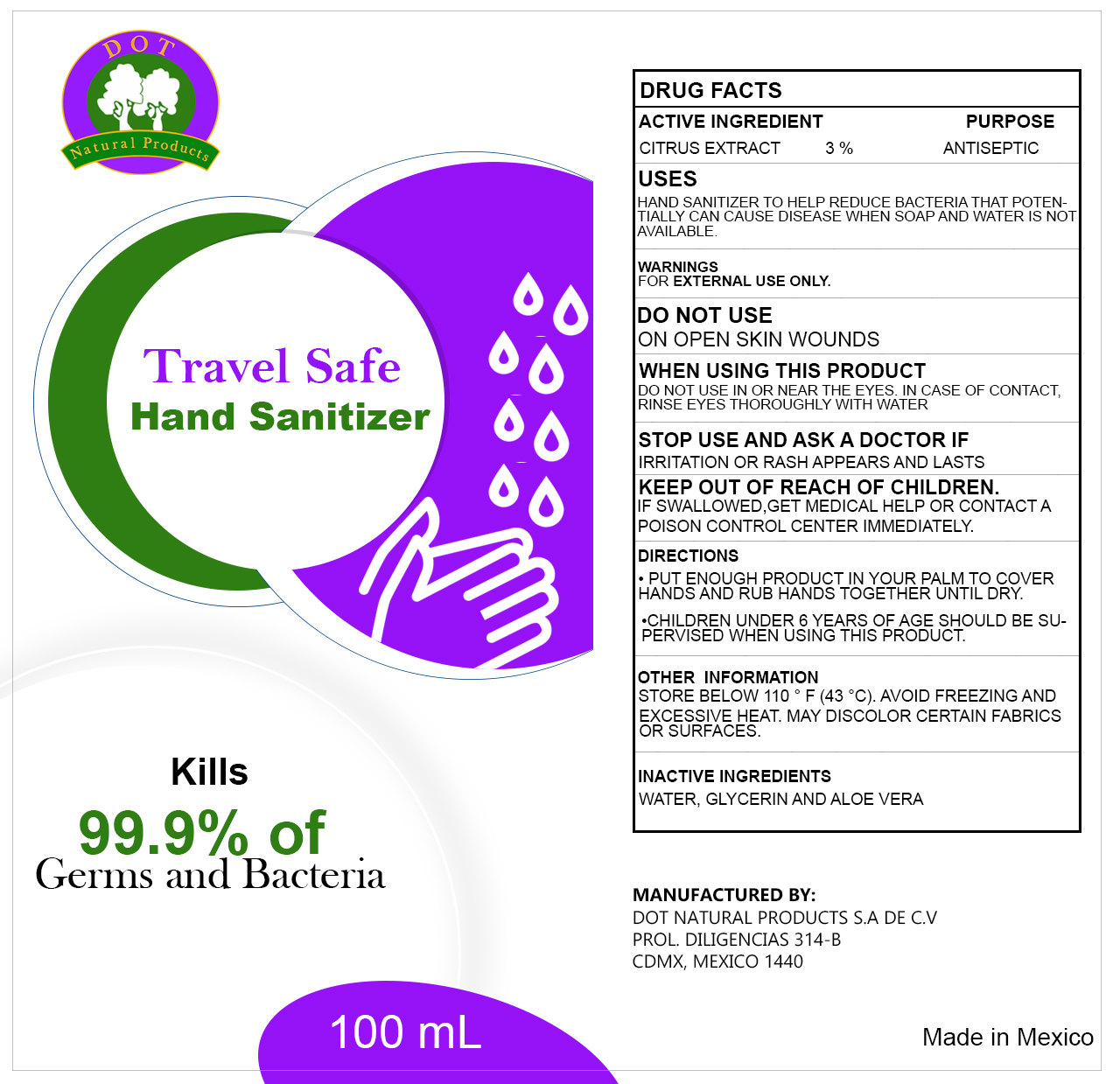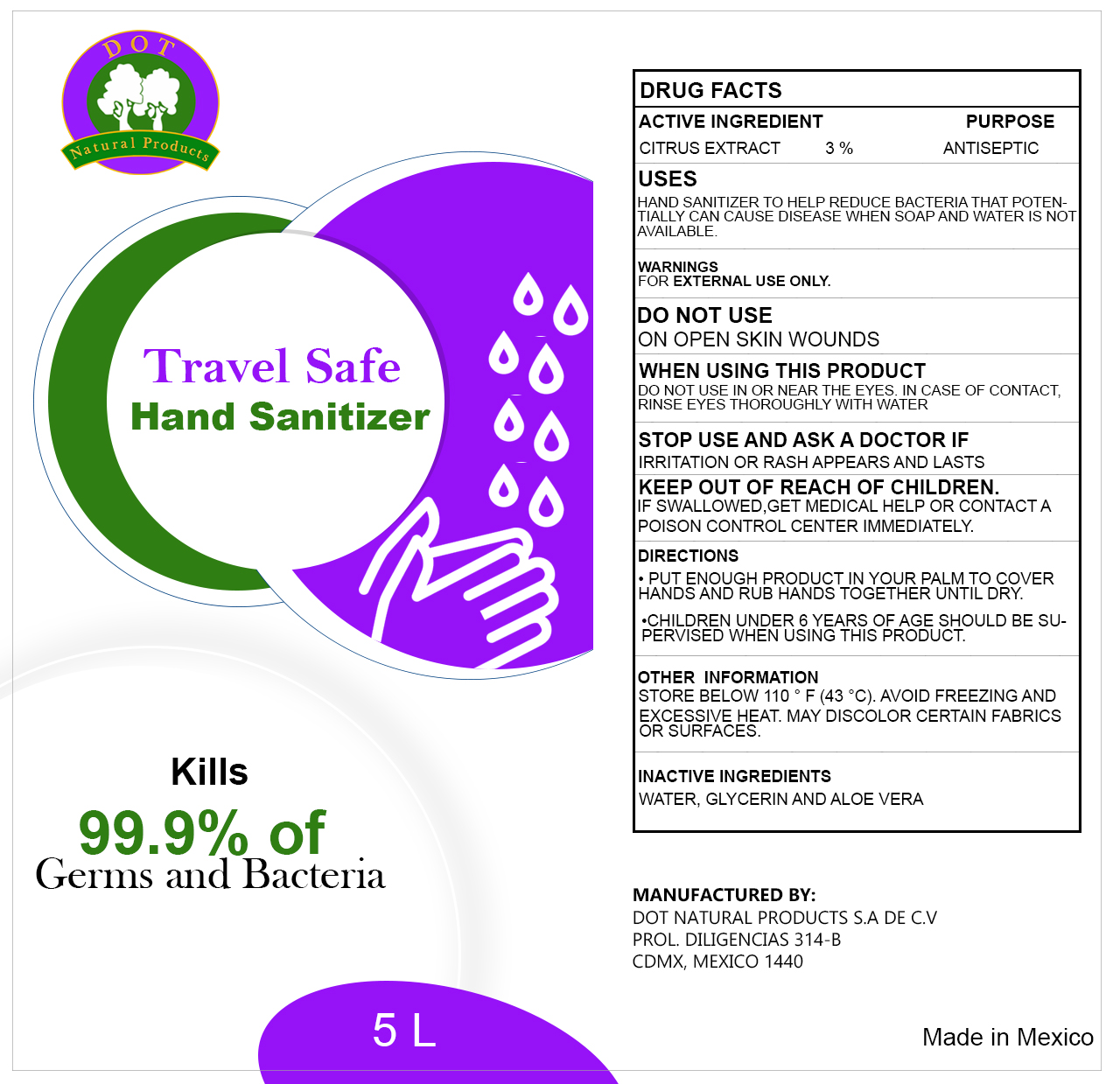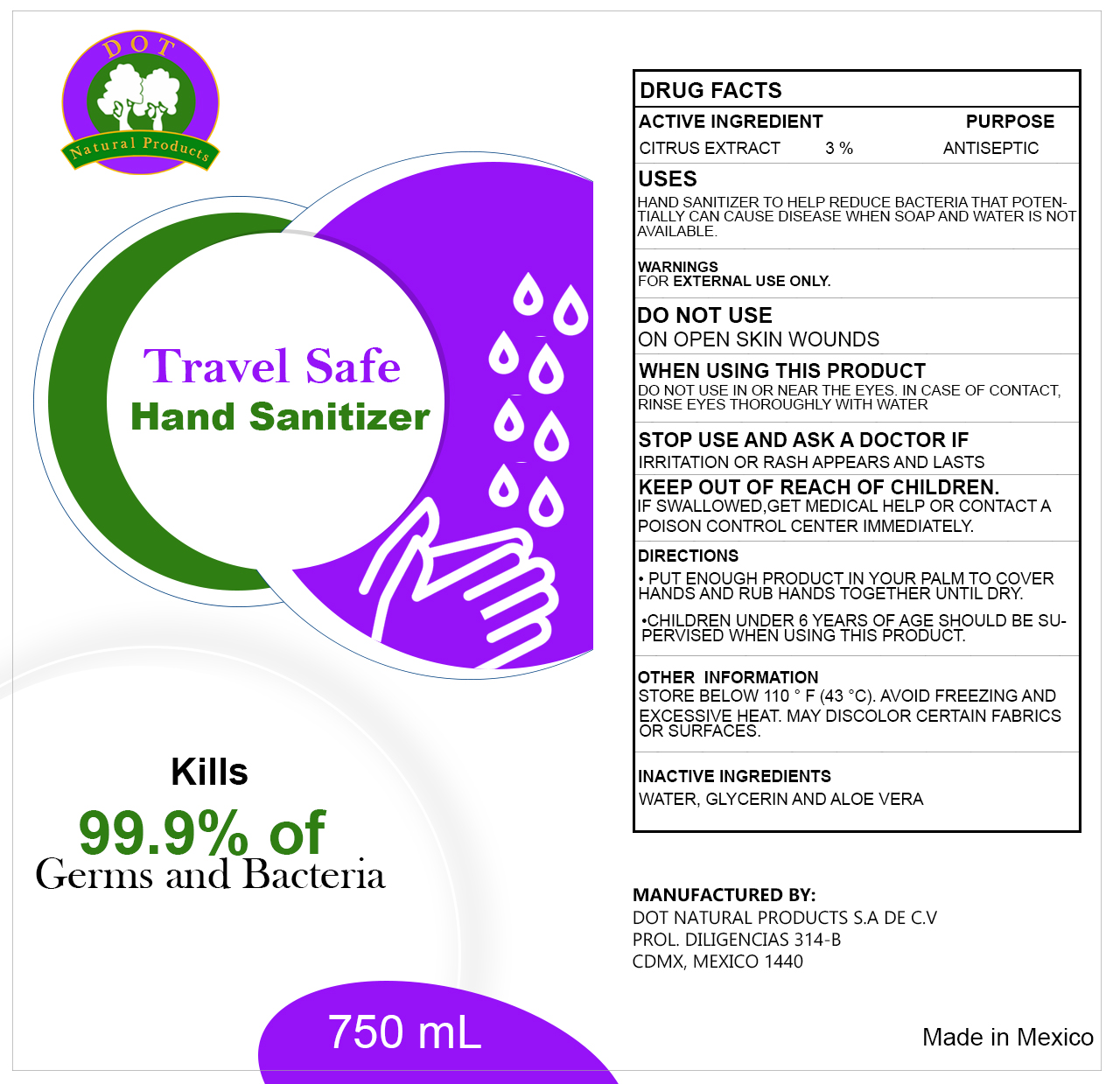 DRUG LABEL: Hand Sanitizer
NDC: 80490-010 | Form: LIQUID
Manufacturer: Dot Natural Products, S.A. de C.V.
Category: otc | Type: HUMAN OTC DRUG LABEL
Date: 20211108

ACTIVE INGREDIENTS: CITRUS JUICE 3 g/100 g
INACTIVE INGREDIENTS: GLYCERIN; ALOE; WATER

Active Ingredient(s)

Citrus Extraxt 3% v/v. Purpose: Antiseptic

Purpose

Antiseptic, Hand Sanitizer

Use

Hand Sanitizer to help reduce bacteria that potentially can cause disease. For use when soap and water are not available.

Warnings

For external use only.

Do not use

- in children less than 2 months of age
- on open skin wounds

When using this product keep out of eyes, ears, and mouth. In case of contact with eyes, rinse eyes thoroughly with water.
Stop use and ask a doctor if irritation or rash occurs. These may be signs of a serious condition.
Keep out of reach of children. If swallowed, get medical help or contact a Poison Control Center right away.

Stop use and ask a doctor if irritation or rash occurs. These may be signs of a serious condition.

Keep out of reach of children. If swallowed, get medical help or contact a Poison Control Center right away.

Directions

- Place enough product on hands to cover all surfaces. Rub hands together until dry.
- Supervise children under 6 years of age when using this product to avoid swallowing.

Other information

- Store between 15-30C (59-86F)
- Avoid freezing and excessive heat above 40C (104F)

Inactive ingredients

glycerin, aloe, purified water USP

Package Label - Principal Display Panel

750 ml NDC: 80490-010-01

100 ml NDC: 80490-010-02

5000 ml NDC: 80490-010-03